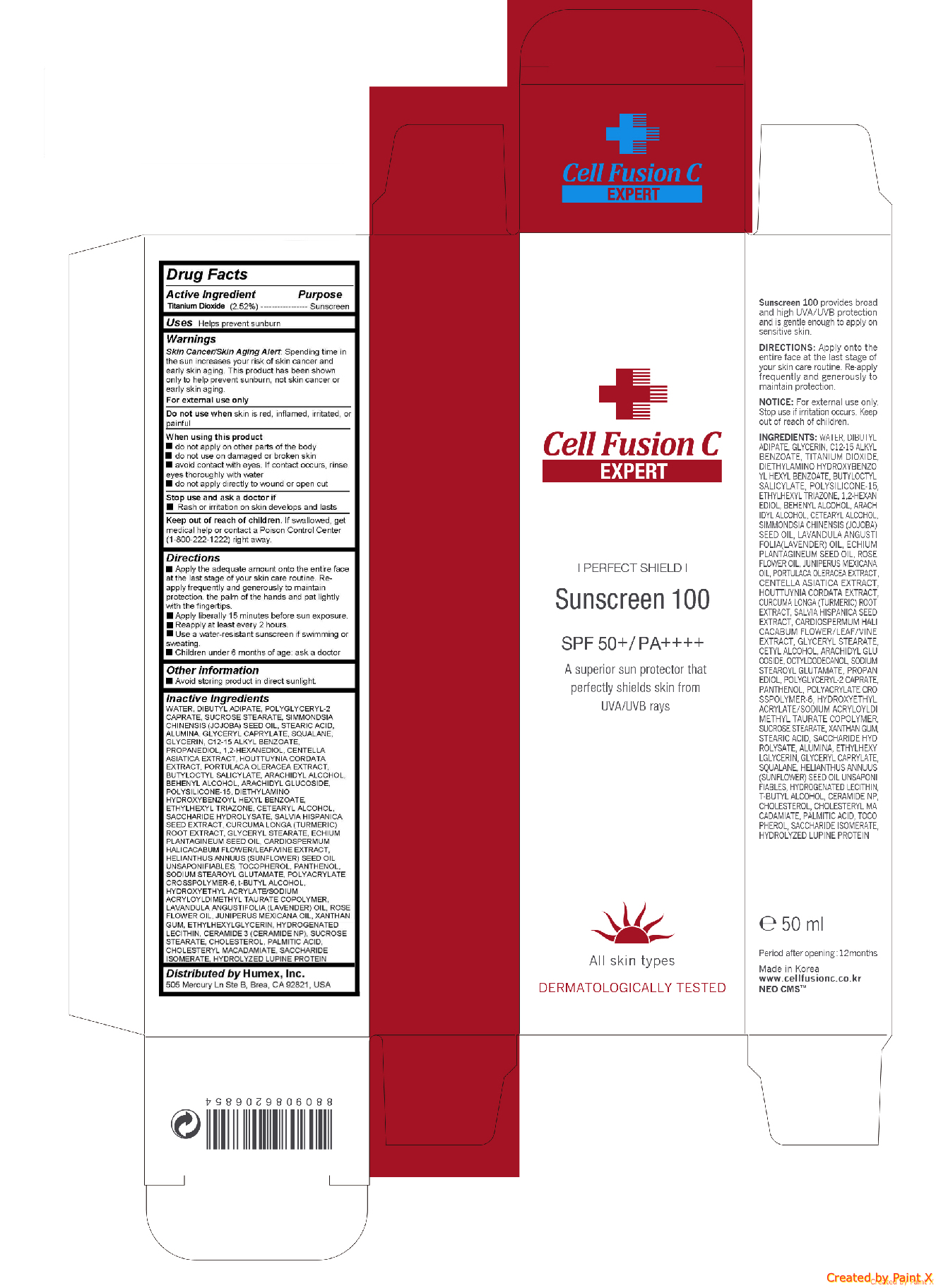 DRUG LABEL: Sunscreen 100
NDC: 52554-1111 | Form: CREAM
Manufacturer: CMS LAB Inc.
Category: otc | Type: HUMAN OTC DRUG LABEL
Date: 20171019

ACTIVE INGREDIENTS: TITANIUM DIOXIDE 1.26 g/50 mL
INACTIVE INGREDIENTS: JOJOBA OIL; STEARIC ACID; GLYCERYL CAPRYLATE; SQUALANE; ALKYL (C12-15) BENZOATE; PROPANEDIOL; 1,2-HEXANEDIOL; ARACHIDYL ALCOHOL; HOUTTUYNIA CORDATA FLOWERING TOP; ALUMINUM OXIDE; GLYCERIN; CENTELLA ASIATICA; ARACHIDYL GLUCOSIDE; BUTYLOCTYL SALICYLATE; DOCOSANOL; PURSLANE; POLYSILICONE-15; DIETHYLAMINO HYDROXYBENZOYL HEXYL BENZOATE; ETHYLHEXYL TRIAZONE; CETOSTEARYL ALCOHOL; SACCHARIDE HYDROLYSATE; CHIA SEED; TURMERIC; WATER; DIBUTYL ADIPATE; SUCROSE STEARATE

Sunscreen 100

Active ingredients

Titamiun Dioxdie (2.52%)

Purpose

Sunscreen

Uses

Helps prevent sunburn

Warnings

Skin Cancer/Skin Aging Alert: Spending time in the sun increases your risk of skin cancer and early skin aging. This product has been shown only to help prevent sunburn, not skin cancer or early skin aging.

For external use only

Do not use when skin is red, inflamed, irritated, or painful

When using this product

- do not apply on other parts of the body

- do not use on damaged or broken skin

- avoid contact with eyes. If contact occurs, rinse eyes thoroughly with water

- do not apply directly to wound or open cut

Stop use and ask a doctor if

- Rash or irritation on skin develops and lasts

Directions

- Apply the adequate amount onto the entire face at the last stage of your skin care routine.

Re-apply frequently and generously to maintain protection. the palm of the hands and pat lightly with the fingertips.

- Apply liberally 15 minutes before sun exposure.

- Reapply at least every 2 hours.

- Use a water-resistant sunscreen if swimming or sweating.

- Children under 6 months of age: ask a doctor

Inactive ingredients

WATER, DIBUTYL ADIPATE, POLYGLYCERYL-2 CAPRATE, SUCROSE STEARATE, SIMMONDSIA CHINENSIS (JOJOBA) SEED OIL, STEARIC ACID, ALUMINA, GLYCERYL CAPRYLATE, SQUALANE, GLYCERIN, C12-15 ALKYL BENZOATE, PROPANEDIOL, 1,2-HEXANEDIOL, CENTELLA ASIATICA EXTRACT, HOUTTUYNIA CORDATA EXTRACT, PORTULACA OLERACEA EXTRACT, BUTYLOCTYL SALICYLATE, ARACHIDYL ALCOHOL, BEHENYL ALCOHOL, ARACHIDYL GLUCOSIDE, POLYSILICONE-15, DIETHYLAMINO HYDROXYBENZOYL HEXYL BENZOATE, ETHYLHEXYL TRIAZONE, CETEARYL ALCOHOL, SACCHARIDE HYDROLYSATE, SALVIA HISPANICA SEED EXTRACT, CURCUMA LONGA (TURMERIC) ROOT EXTRACT, GLYCERYL STEARATE, ECHIUM PLANTAGINEUM SEED OIL, CARDIOSPERMUM HALICACABUM FLOWER/LEAF/VINE EXTRACT, HELIANTHUS ANNUUS (SUNFLOWER) SEED OIL UNSAPONIFIABLES, TOCOPHEROL, PANTHENOL, SODIUM STEAROYL GLUTAMATE, POLYACRYLATE CROSSPOLYMER-6, t-BUTYL ALCOHOL, HYDROXYETHYL ACRYLATE/SODIUM ACRYLOYLDIMETHYL TAURATE COPOLYMER, LAVANDULA ANGUSTIFOLIA (LAVENDER) OIL, ROSE FLOWER OIL, JUNIPERUS MEXICANA OIL, XANTHAN GUM, ETHYLHEXYLGLYCERIN, HYDROGENATED LECITHIN, CERAMIDE 3 (CERAMIDE NP), SUCROSE STEARATE, CHOLESTEROL, PALMITIC ACID, CHOLESTERYL MACADAMIATE, SACCHARIDE ISOMERATE, HYDROLYZED LUPINE PROTEIN